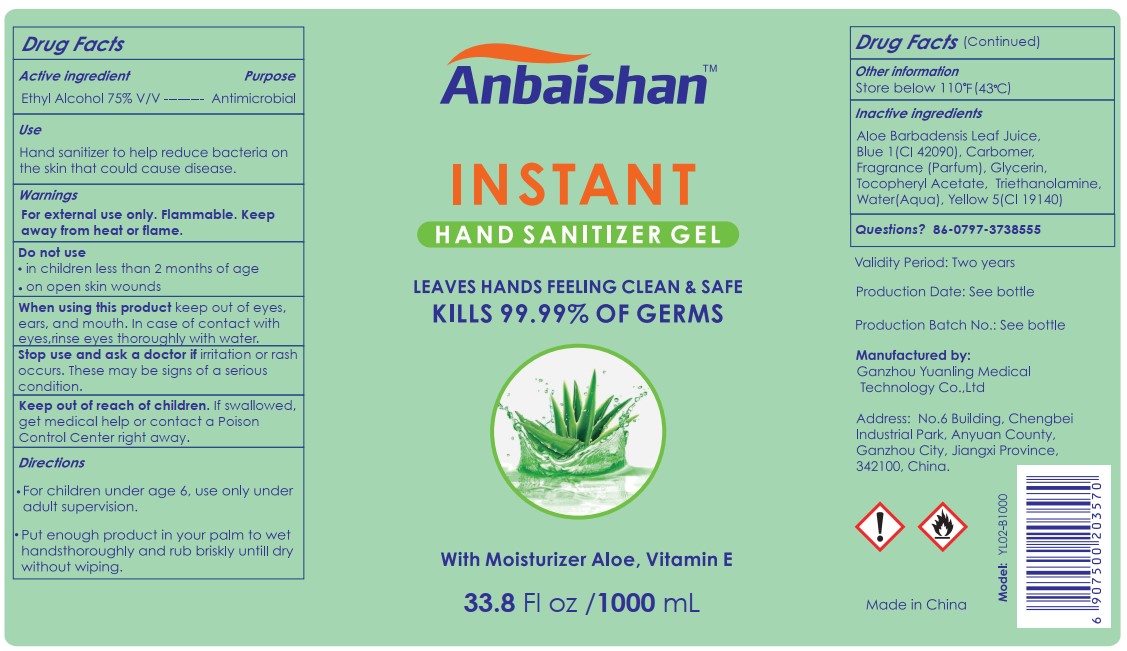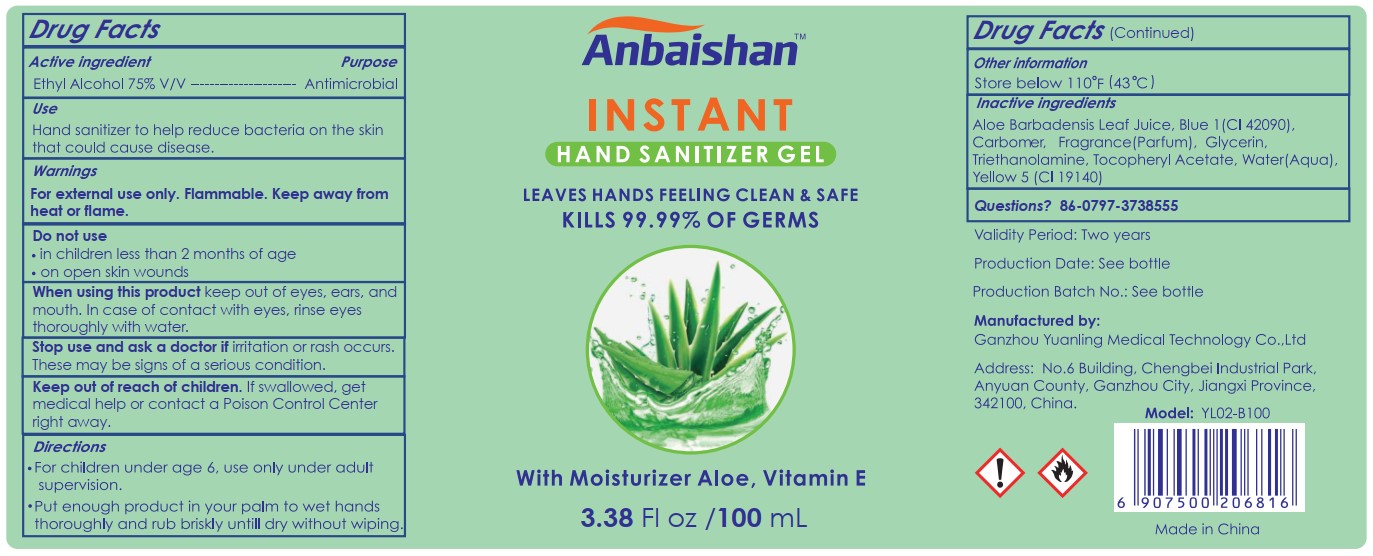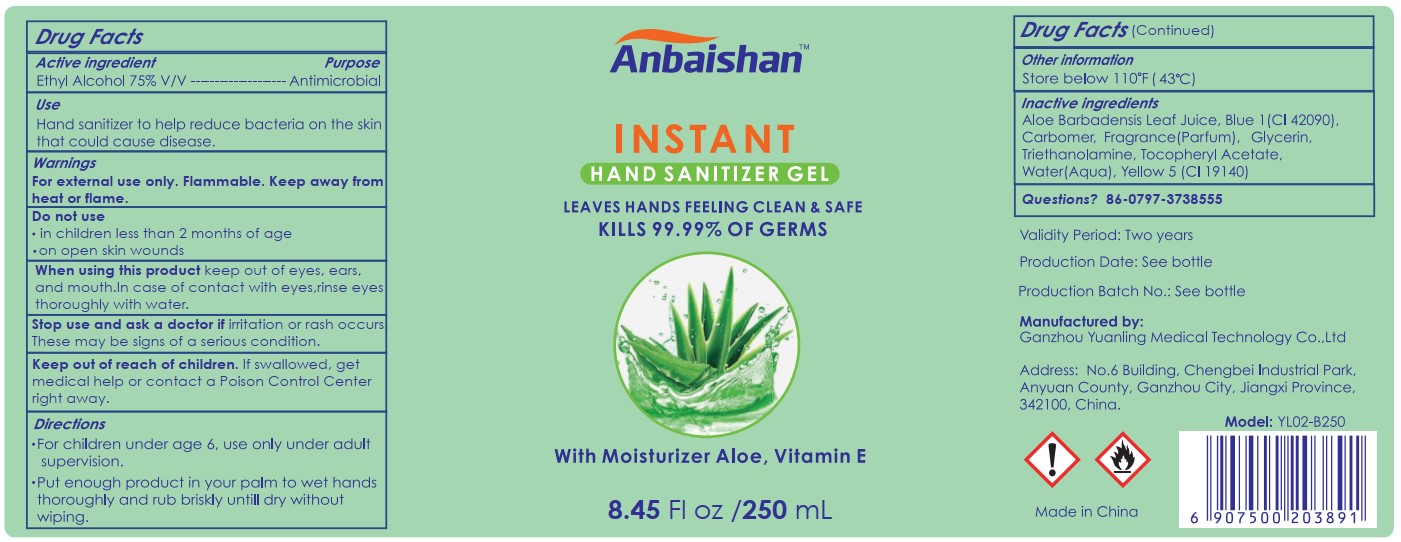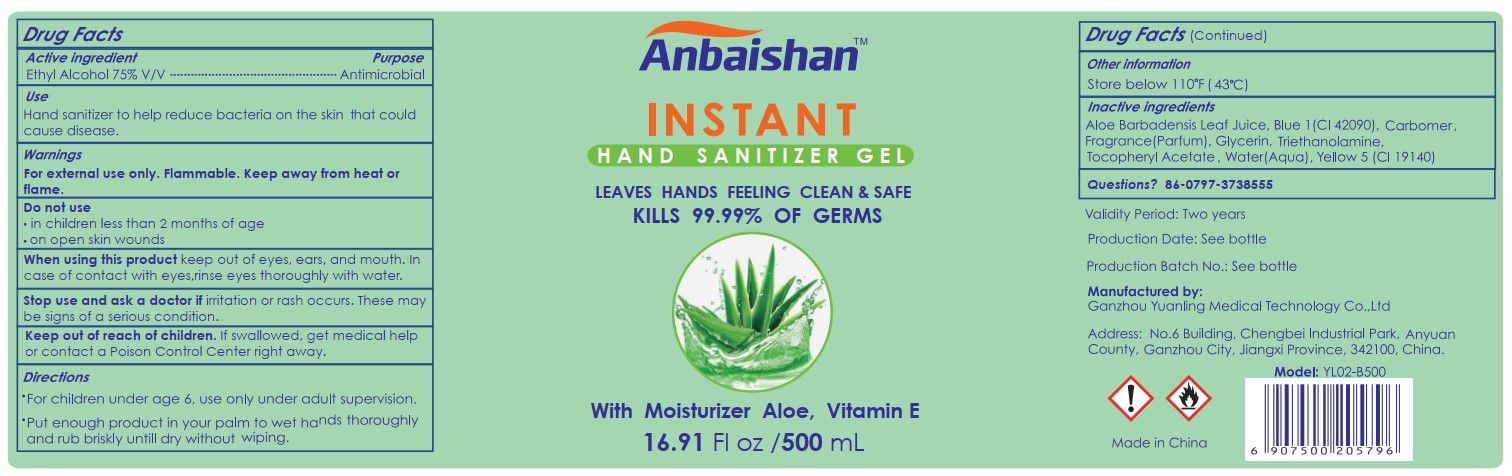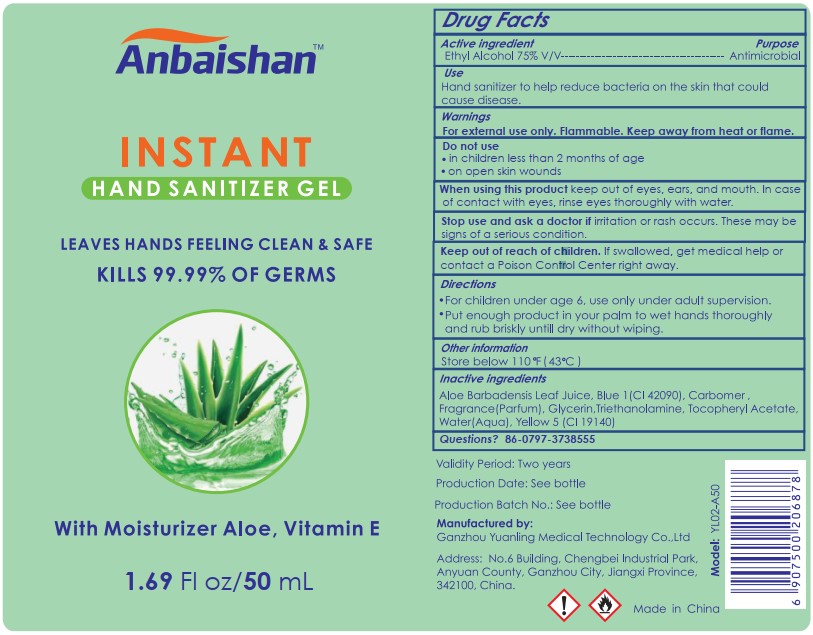 DRUG LABEL: Instant Hand Sanitizer Gel
NDC: 78301-050 | Form: GEL
Manufacturer: Ganzhou Yuanling Medical Technology Co.,ltd
Category: otc | Type: HUMAN OTC DRUG LABEL
Date: 20200609

ACTIVE INGREDIENTS: ALCOHOL 75 mL/100 mL
INACTIVE INGREDIENTS: FRAGRANCE LAVENDER & CHIA F-153480 0.03 mL/100 mL; FD&C BLUE NO. 1 0.00003 mL/100 mL; .ALPHA.-TOCOPHEROL ACETATE 0.001 mL/100 mL; ALOE 0.01 mL/100 mL; FD&C YELLOW NO. 5 0.00009 mL/100 mL; TROLAMINE 0.067 mL/100 mL; GLYCERIN 0.5 mL/100 mL; CARBOMER 980 0.176 mL/100 mL; WATER 24.21588 mL/100 mL

Active Ingredient(s)

Ethyl Alcohol 75% v/v. Purpose: Antimicrobial

Purpose

Antimicrobial, Hand Sanitizer

Use

Hand sanitizer to help reduce bacteria on the skin that could cause disease.

Warnings

For external use only. Flammable. Keep away from heat or flame

Do not use

- in children less than 2 months of age
- on open skin wounds

When using this product keep out of eyes, ears, and mouth. In case of contact with eyes, rinse eyes thoroughly with water.
Stop use and ask a doctor if irritation or rash occurs. These may be signs of a serious condition.
Keep out of reach of children. If swallowed, get medical help or contact a Poison Control Center right away.

Stop use and ask a doctor if irritation or rash occurs. These may be signs of a serious condition.

Keep out of reach of children. If swallowed, get medical help or contact a Poison Control Center right away.

Directions

- For children under age 6, use only under adult supervision.
- Put enough product in your palm to wet hands thoroughly and rub briskly untill dry without wiping.

Other information

- Store below 110℉ (43 ℃)

Inactive ingredients

Aloe Barbadensis Leaf Juice, Blue 1(CI 42090), Carbomer, Fragrance (Parfum), Glycerin, Triethanolamine, Tocopheryl Acetate, Water(Aqua), Yellow 5 (CI 19140)

Package Label - Principal Display Panel

50 mL NDC: 78301-050-01

Package Label - Principal Display Panel

100 mL NDC: 78301-050-02

Package Label - Principal Display Panel

250 mL NDC: 78301-050-05

Package Label - Principal Display Panel

500 mL NDC: 78301-050-10

Package Label - Principal Display Panel

1000 mL NDC:78301-050-20